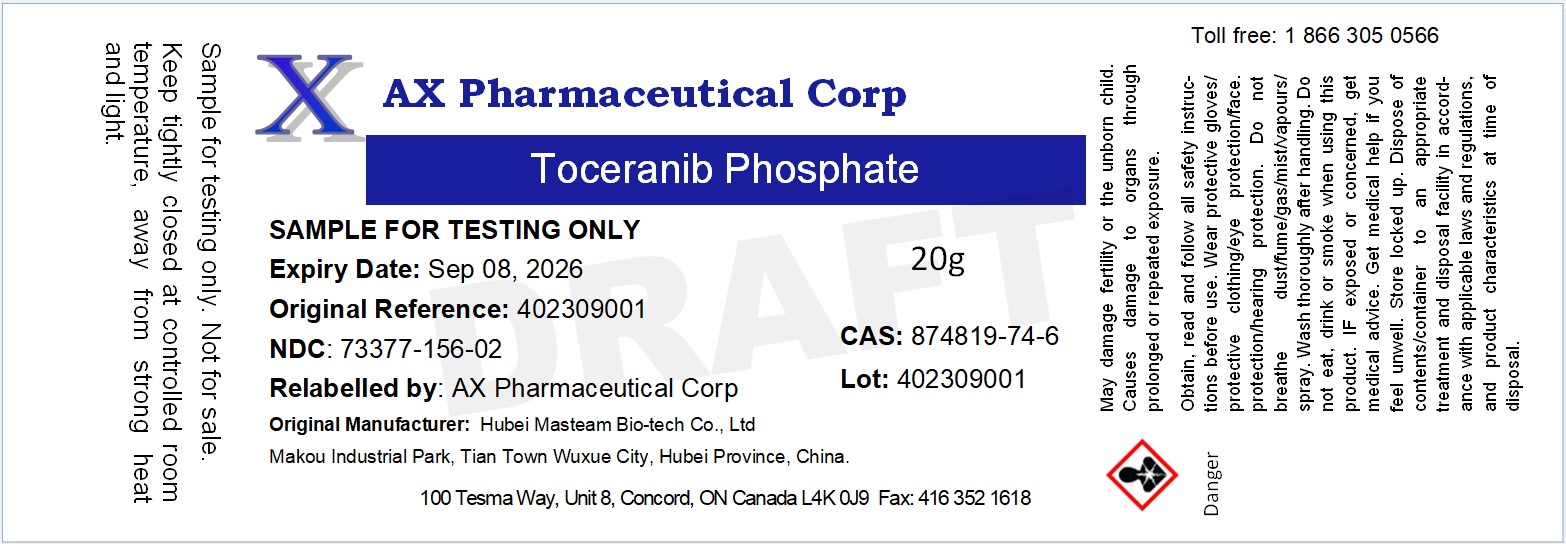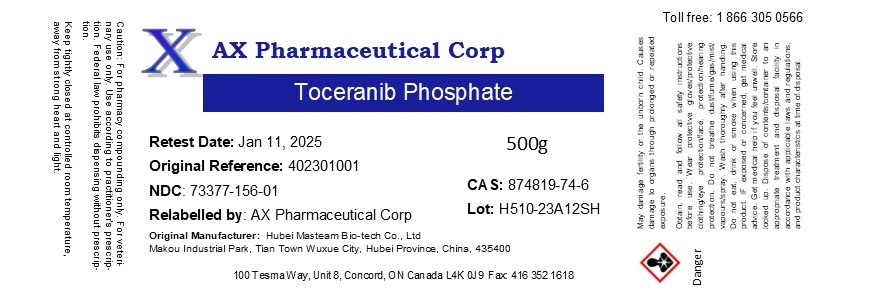 DRUG LABEL: Toceranib Phosphate
NDC: 73377-156 | Form: POWDER
Manufacturer: AX Pharmaceutical Corp
Category: other | Type: BULK INGREDIENT - ANIMAL DRUG
Date: 20260116

ACTIVE INGREDIENTS: TOCERANIB PHOSPHATE 1 g/1 g

Toceranib Phosphate